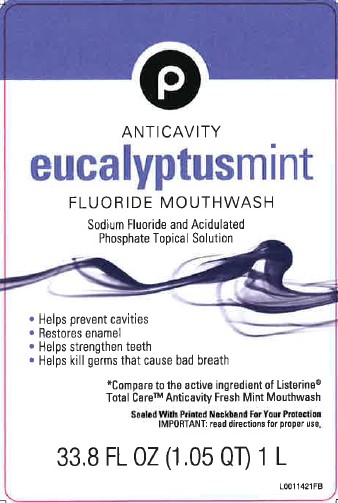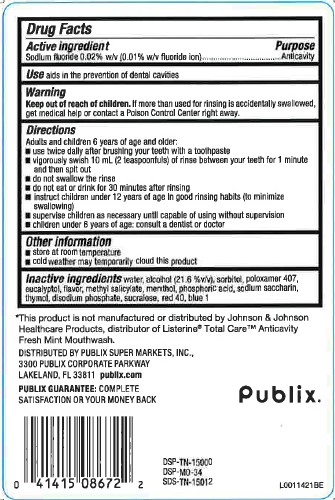 DRUG LABEL: Anticavity Fluoride Rinse
NDC: 56062-163 | Form: MOUTHWASH
Manufacturer: Publix Super Markets, Inc.
Category: otc | Type: HUMAN OTC DRUG LABEL
Date: 20260205

ACTIVE INGREDIENTS: SODIUM FLUORIDE 1 mg/1 mL
INACTIVE INGREDIENTS: WATER; ALCOHOL; SORBITOL; POLOXAMER 407; EUCALYPTOL; METHYL SALICYLATE; MENTHOL; PHOSPHORIC ACID; SACCHARIN SODIUM; THYMOL; SODIUM PHOSPHATE, DIBASIC, ANHYDROUS; SUCRALOSE; FD&C RED NO. 40; FD&C BLUE NO. 1

Publix 163.005/163AF
Anticavity Fluoride Mouthwash

Active ingredient

Sodium fluoride 0.02% w/v (0.01% w/v fluoride ion)

Purpose

Anticavity

Use

aids in the prevention of dental cavities

Warnings

for this product

Keep out of reach of children.

If more than used for rinsing is accidentally swallowed, get medical help or contact a Poison Control Center right away.

Directions

Adults and children 12 years of age and older:

- use twice daily after brushing your teeth with toothpaste
- vigorously swish 10 mL (2 teaspoonfuls) of rinse between your teeth for 1 minute and then spit out
- do not swallow the rinse
- do not eat or drink for 30 minutes after rinsing
- instruct children under 12 years of age in good rinsing habits (to minimize swallowing)
- supervise children as necessary until capable of using without supervision
- children under 12 years of age: consult a dentist or doctor

Other information

- store at room temperature
- cold weather may temporarily cloud this product

Inactive ingredients

water, alcohol (21.6 %v/v), sorbitol, poloxamer 407, eucalyptol, flavor, methyl salicylate, menthol, phosphoric acid, sodium saccharin, thymol, disodium phosphate, sucralose, red 40, blue 1

Disclaimer

*This product is not manufactured or distributed by Johnson & Johnson Healthcare Products, distributor of Listerine®Total Care™ Anticavity Fresh Mint Mouthwash.

ADVERSE REACTION

DISTRIBUTED BY PUBLIX SUPER MARKETS, INC.,

3300 PUBLIX CORPORATE PARKWAY

LAKELAND, FL 33811 publix.com

PUBLIX GUARANTEE: COMPLETE SATISFACTION OR YOUR MONEY BACK

PUBLIX®

DSP-TN-15000

DSP-MO-34

SDS-TN-15012

principal display panel

P

ANTICAVITY

EUCALYPTUS MINT

FLUORIDE MOUTHWASH

Sodium Fluoride and Acidulated Phosphate Topical Solution

- Helps prevent cavities
- Restores enamel
- Helps strengthen teeth
- Helps kill germs that cause bad breath

*Compare to the active ingredient OF Listerine®Total Care™ Anticavity Fresh Mint Mouthwash

SEALED WITH PRINTED NECKBAND FOR YOUR PROTECTION

IMPORTANT: READ DIRECTIONS FOR PROPER USE.

33.8 FL OZ (1.05 QT) 1 L